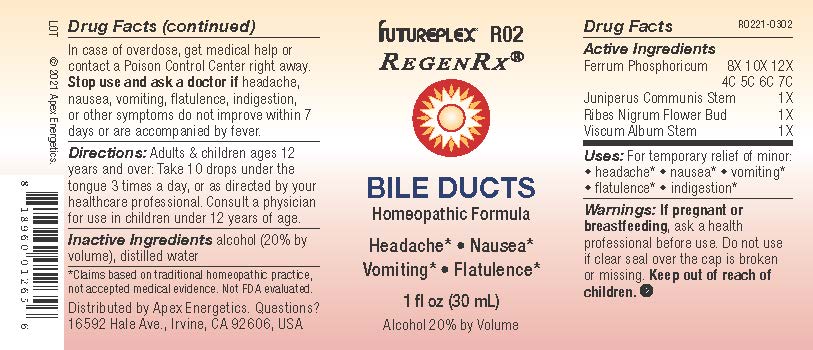 DRUG LABEL: R02
NDC: 63479-1802 | Form: SOLUTION/ DROPS
Manufacturer: Apex Energetics Inc.
Category: homeopathic | Type: HUMAN OTC DRUG LABEL
Date: 20240108

ACTIVE INGREDIENTS: FERROSOFERRIC PHOSPHATE 7 [hp_C]/1 mL; JUNIPERUS COMMUNIS STEM 1 [hp_X]/1 mL; RIBES NIGRUM FLOWER BUD 1 [hp_X]/1 mL; VISCUM ALBUM STEM 1 [hp_X]/1 mL
INACTIVE INGREDIENTS: ALCOHOL; WATER

R02

Active Ingredients
Ferrum Phosphoricum | 8X 10X 12X 4C 5C 6C 7C
Juniperus Communis Stem | 1X
Ribes Nigrum Flower Bud | 1X
Viscum Album Stem | 1X

INDICATIONS AND USAGE

Uses:

For temporary relief of minor:

headache*

nausea*

vomiting*

flatulence*

indigestion*

*Claims based on traditional homeopathic practice, not accepted medical evidence. Not FDA evaluated.

Warnings:

PREGNANCY OR BREAST FEEDING

If pregnant or breastfeeding, ask a health professional before use.

Do not use if clear seal over the cap is broken or missing.

Keep out of reach of children. In case of overdose, get medical help or contact a Poison Control Center right away.

Stop use and ask a doctor if headache, nausea, vomiting, flatulence, indigestion, or other symptoms do not improve within 7 days or are accompanied by fever.

Directions:

Adults & children ages 12 years and over: Take 10 drops under the tongue 3 times a day, or as directed by your healthcare professional. Consult a physician for use in children under 12 years of age.

Inactive Ingredients

alcohol (20% by volume), distilled water

Distributed by Apex Energetics. Questions?

16592 Hale Ave., Irvine, CA 92606, USA

PACKAGE LABEL

FUTUREPLEX® R02

REGENRX®

BILE DUCTS

Homeopathic Formula

Headache*

Nausea*

Vomiting*

Flatulence*

1 fl oz (30 mL)

Alcohol 20% by Volume